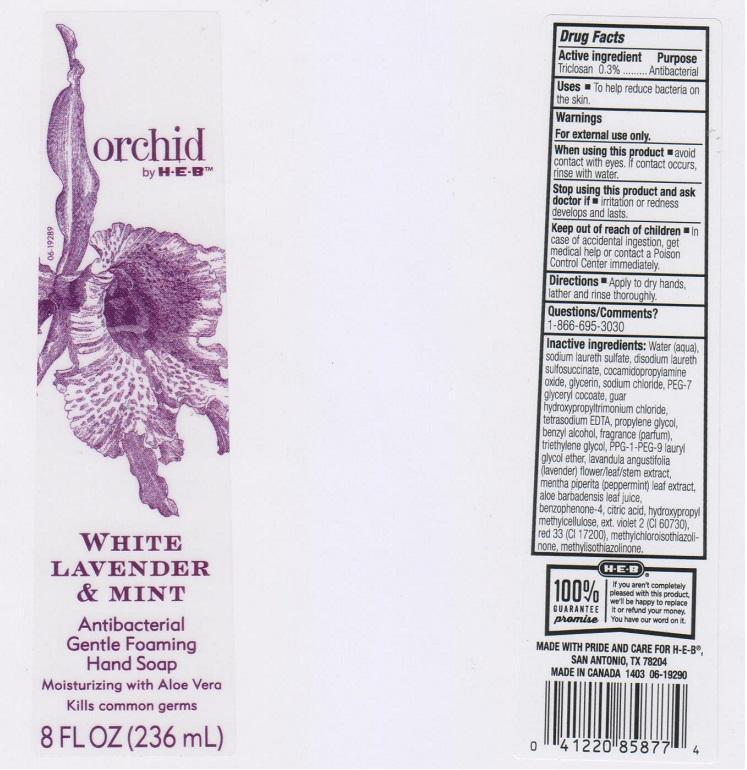 DRUG LABEL: ORCHID BY H E B
NDC: 37808-081 | Form: LIQUID
Manufacturer: H E B
Category: otc | Type: HUMAN OTC DRUG LABEL
Date: 20141219

ACTIVE INGREDIENTS: TRICLOSAN 3 mg/1 mL
INACTIVE INGREDIENTS: WATER; SODIUM LAURETH SULFATE; DISODIUM LAURETH SULFOSUCCINATE; COCAMIDOPROPYLAMINE OXIDE; GLYCERIN; SODIUM CHLORIDE; PEG-7 GLYCERYL COCOATE; GUAR HYDROXYPROPYLTRIMONIUM CHLORIDE (1.7 SUBSTITUENTS PER SACCHARIDE); EDETATE SODIUM; PROPYLENE GLYCOL; BENZYL ALCOHOL; TRIETHYLENE GLYCOL; PPG-1-PEG-9 LAURYL GLYCOL ETHER; LAVANDULA ANGUSTIFOLIA FLOWERING TOP; MENTHA PIPERITA LEAF; ALOE VERA LEAF; SULISOBENZONE; CITRIC ACID MONOHYDRATE; HYPROMELLOSES; EXT. D&C VIOLET NO. 2; D&C RED NO. 33; METHYLCHLOROISOTHIAZOLINONE; METHYLISOTHIAZOLINONE

DRUG FACTS

ACTIVE INGREDIENT

TRICLOSAN 0.3%

PURPOSE

ANTIBACTERIAL

USES

TO HELP REDUCE BACTERIA ON THE SKIN

WARNINGS

FOR EXTERNAL USE ONLY

WHEN USING THIS PRODUCT

AVOID CONTACT WITH EYES. IF CONTACT OCCURS, RINSE WITH WATER

STOP USING THIS PRODUCT AND ASK DOCTOR IF

IRRITATION OR REDNESS DEVELOPS AND LASTS

KEEP OUT OF REACH OF CHILDREN

IN CASE OF ACCIDENTAL INGESTION, GET MEDICAL HELP OR CONTACT A POISON CONTROL CENTER IMMEDIATELY

DIRECTIONS

APPLY TO DRY HANDS, LATHER AND RINSE THOROUGHLY

QUESTIONS/COMMENTS?

1-866-695-3030

INACTIVE INGREDIENTS

WATER (AQUA), SODIUM LAURETH SULFATE, DISODIUM LAURETH SULFOSUCCINATE, COCAMIDOPROPYLAMINE OXIDE, GLYCERIN, SODIUM CHLORIDE, PEG-7 GLYCERYL COCOATE, GUAR HYDROXYPROPYLTRIMONIUM CHLORIDE, TETRASODIUM EDTA, PROPYLENE GLYCOL, BENZYL ALCOHOL, FRAGRANCE (PARFUM), TRIETHYLENE GLYCOL, PPG-1-PEG-9 LAURYL GLYCOL ETHER, LAVANDULA ANGUSTIFOLIA (LAVENDER) FLOWER/LEAF/STEM EXTRACT, MENTHA PIPERITA (PEPPERMINT) LEAF EXTRACT, ALOE BARBADENSIS LEAF JUICE, BENZOPHENONE-4, CITRIC ACID, HYDROXYPROPYL METHYLCELLULOSE, EXT. VIOLET 2 (CI 60730), RED 33 (CI 17200), METHYLCHLOROISOTHIAZOLINONE, METHYLISOTHIAZOLINONE.